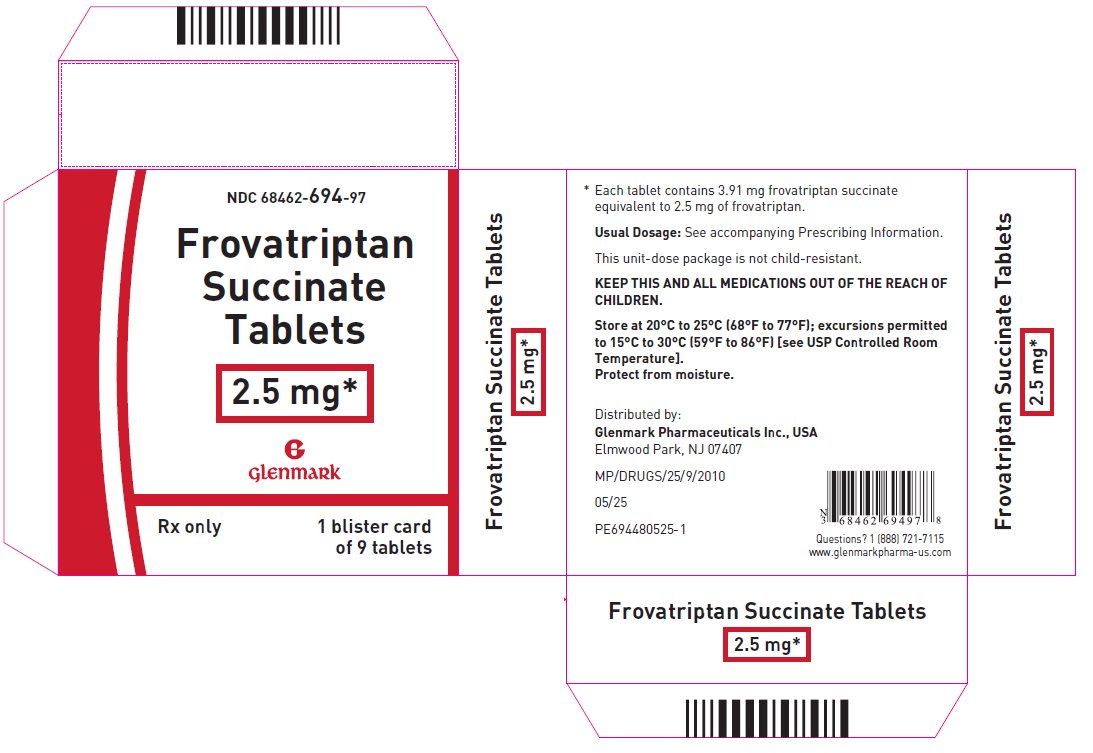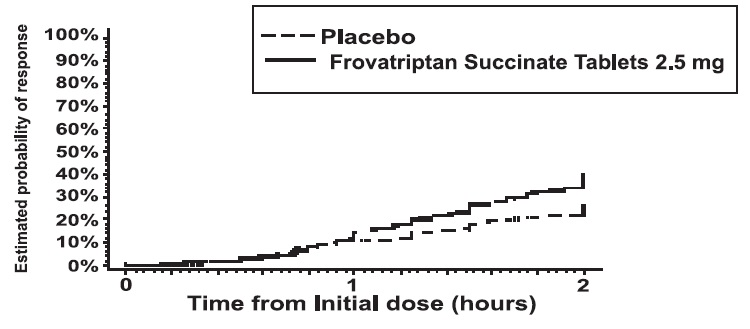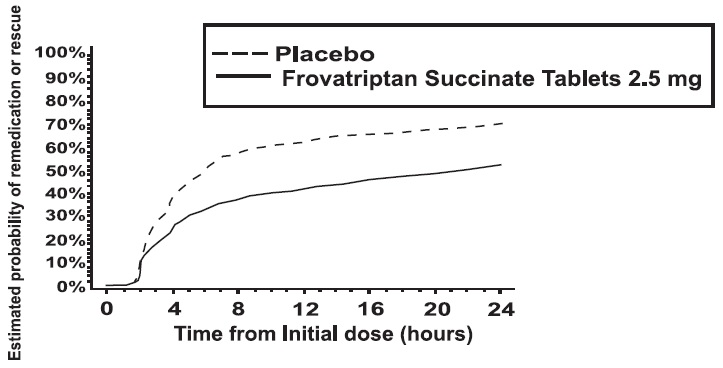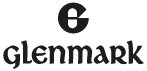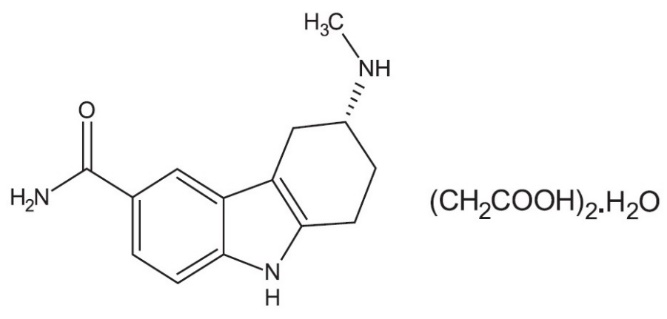 DRUG LABEL: frovatriptan succinate
NDC: 68462-694 | Form: TABLET, FILM COATED
Manufacturer: Glenmark Pharmaceuticals Inc., USA
Category: prescription | Type: HUMAN PRESCRIPTION DRUG LABEL
Date: 20260128

ACTIVE INGREDIENTS: FROVATRIPTAN SUCCINATE 2.5 mg/1 1
INACTIVE INGREDIENTS: ANHYDROUS LACTOSE; SILICON DIOXIDE; HYPROMELLOSE, UNSPECIFIED; LACTOSE MONOHYDRATE; MAGNESIUM STEARATE; MICROCRYSTALLINE CELLULOSE; SODIUM STARCH GLYCOLATE TYPE A POTATO; TALC; TITANIUM DIOXIDE; TRIACETIN

HIGHLIGHTS OF PRESCRIBING INFORMATION

These highlights do not include all the information needed to use FROVATRIPTAN SUCCINATE TABLETS safely and effectively. See full prescribing information for FROVATRIPTAN SUCCINATE TABLETS.
FROVATRIPTAN SUCCINATE tablets, for oral use
Initial U.S. Approval: 2001

1 INDICATIONS AND USAGE

Frovatriptan succinate is a serotonin (5-HT1B/1D) receptor agonist (triptan) indicated for the acute treatment of migraine with or without aura in adults (1)

Limitations of Use

- Use only after a clear diagnosis of migraine has been established (1)
- Not indicated for the prophylactic therapy of migraine (1)
- Not indicated for the treatment of cluster headache (1)

2 DOSAGE AND ADMINISTRATION

- 1 tablet taken with fluids. Second tablet may be taken 2 hours after initial dose if headache recurs following initial relief. Total dose not to exceed 3 tablets in any 24-hour period (2)

3 DOSAGE FORMS AND STRENGTHS

Tablets: 2.5 mg (3)

4 CONTRAINDICATIONS

- History of coronary artery disease or coronary artery vasospasm (4)
- Wolff-Parkinson-White syndrome or other cardiac accessory conduction pathway disorders (4)
- History of stroke, transient ischemic attack, or hemiplegic or basilar migraine (4)
- Peripheral vascular disease (4)
- Ischemic bowel disease (4)
- Uncontrolled hypertension (4)
- Recent (within 24 hours) use of treatment with another 5-HT1 agonist, or an ergotamine-containing medication (4)
- Hypersensitivity to frovatriptan succinate (angioedema and anaphylaxis seen) (4)

5 WARNINGS AND PRECAUTIONS

- Myocardial ischemia/infarction or Prinzmetal’s angina: Perform cardiac evaluation in patients with multiple cardiovascular risk factors (5.1)
- Arrhythmias: Discontinue frovatriptan succinate if occurs (5.2)
- Chest/throat/neck/jaw pain, tightness, pressure, or heaviness: Generally not associated with myocardial ischemia; evaluate high risk patients for coronary artery disease (5.3)
- Cerebral hemorrhage, subarachnoid hemorrhage, and stroke: Discontinue frovatriptan succinate if occurs (5.4)
- Gastrointestinal ischemic reactions and peripheral vasospastic reactions: Discontinue frovatriptan succinate if occurs (5.5)
- Medication overuse headache: Detoxification may be necessary (5.6)
- Serotonin syndrome: Discontinue frovatriptan succinate if occurs (5.7, 7.3)

6 ADVERSE REACTIONS

- Most common adverse reactions (≥2% and >placebo) were dizziness, headache, paresthesia, dry mouth, dyspepsia, fatigue, hot or cold sensation, chest pain, skeletal pain, and flushing (6.1)

To report SUSPECTED ADVERSE REACTIONS, contact Glenmark Pharmaceuticals Inc., USA at 1 (888) 721-7115 or FDA at 1-800-FDA-1088 or www.fda.gov/medwatch.

8 USE IN SPECIFIC POPULATIONS

- Pregnancy: Based on animal data, may cause fetal harm (8.1)

FULL PRESCRIBING INFORMATION

1 INDICATIONS AND USAGE

Frovatriptan succinate tablets are indicated for the acute treatment of migraine with or without aura in adults.

Limitations of Use

- Use only if a clear diagnosis of migraine has been established. If a patient has no response for the first migraine attack treated with frovatriptan succinate tablets, reconsider the diagnosis of migraine before frovatriptan succinate tablets are administered to treat any subsequent attacks.
- Frovatriptan succinate tablets are not indicated for the prevention of migraine attacks.
- Safety and effectiveness of frovatriptan succinate tablets have not been established for cluster headache.

2 DOSAGE AND ADMINISTRATION

Dosing Information

The recommended dose is a single tablet of frovatriptan succinate (frovatriptan 2.5 mg) taken orally with fluids.

If the migraine recurs after initial relief, a second tablet may be taken, providing there is an interval of at least 2 hours between doses. The total daily dose of frovatriptan succinate tablets should not exceed 3 tablets (3 × 2.5 mg per 24-hour period).

There is no evidence that a second dose of frovatriptan succinate tablets is effective in patients who do not respond to a first dose of the drug for the same headache.

The safety of treating an average of more than 4 migraine attacks in a 30-day period has not been established.

3 DOSAGE FORMS AND STRENGTHS

2.5 mg Tablets: White to off-white, circular biconvex film-coated tablets, debossed with ‘72’ on one side and ‘G’ on the other side.

4 CONTRAINDICATIONS

Frovatriptan succinate tablets are contraindicated in patients with:

- Ischemic coronary artery disease (CAD) (e.g., angina pectoris, history of myocardial infarction, or documented silent ischemia), or coronary artery vasospasm, including Prinzmetal’s angina [see Warnings and Precautions (5.1)].
- Wolff-Parkinson-White Syndrome or arrhythmias associated with other cardiac accessory conduction pathway disorders [see Warnings and Precautions (5.2)].
- History of stroke, transient ischemic attack (TIA), or history of hemiplegic or basilar migraine because these patients are at a higher risk of stroke [see Warnings and Precautions (5.4)].
- Peripheral vascular disease [see Warnings and Precautions (5.5)].
- Ischemic bowel disease [see Warnings and Precautions (5.5)].
- Uncontrolled hypertension [see Warnings and Precautions (5.8)].
- Recent use (i.e., within 24 hours) of another 5-HT1 agonist, an ergotamine containing or ergot-type medication such as dihydroergotamine (DHE) or methysergide [see Drug Interactions (7.1, 7.2)].
- Hypersensitivity to frovatriptan succinate tablets (angioedema and anaphylaxis seen) [see Warnings and Precautions (5.9)].

5 WARNINGS AND PRECAUTIONS

5.1 Myocardial Ischemia, Myocardial Infarction, and Prinzmetal’s Angina

Frovatriptan succinate tablets are contraindicated in patients with ischemic or vasospastic CAD. There have been rare reports of serious cardiac adverse reactions, including acute myocardial infarction, occurring within a few hours following administration of frovatriptan. Some of these reactions occurred in patients without known CAD. Frovatriptan may cause coronary artery vasospasm (Prinzmetal’s angina), even in patients without a history of CAD.

Perform a cardiovascular evaluation in triptan-naïve patients who have multiple cardiovascular risk factors (e.g., increased age, diabetes, hypertension, smoking, obesity, strong family history of CAD) prior to receiving frovatriptan. Do not administer frovatriptan if there is evidence of CAD or coronary artery vasospasm [see Contraindications (4)]. For patients with multiple cardiovascular risk factors who have a negative cardiovascular evaluation, consider administrating the first frovatriptan dose in a medically-supervised setting and performing an electrocardiogram (ECG) immediately following frovatriptan administration. For such patients, consider periodic cardiovascular evaluation in intermittent long-term users of frovatriptan.

5.2 Arrhythmias

Life-threatening disturbances of cardiac rhythm including ventricular tachycardia and ventricular fibrillation leading to death have been reported within a few hours following the administration of 5-HT1 agonists. Discontinue frovatriptan if these disturbances occur. Frovatriptan succinate tablets are contraindicated in patients with Wolff-Parkinson-White syndrome or arrhythmias associated with other cardiac accessory conduction pathway disorders [see Contraindications (4)].

5.3 Chest, Throat, Neck, and Jaw Pain/Tightness/Pressure

Sensations of pain, tightness, pressure, and heaviness have been reported in the chest, throat, neck, and jaw after treatment with frovatriptan and are usually non-cardiac in origin. However, perform a cardiac evaluation if these patients are at high cardiac risk. The use of frovatriptan succinate tablets are contraindicated in patients with CAD and those with Prinzmetal’s angina [see Contraindications (4)].

5.4 Cerebrovascular Events

Cerebral hemorrhage, subarachnoid hemorrhage, stroke, and other cerebrovascular events have been reported in patients treated with 5-HT1 agonists, and some have resulted in fatalities. In a number of cases, it appears possible that the cerebrovascular events were primary, the agonist having been administered in the incorrect belief that the symptoms experienced were a consequence of migraine, when they were not.

Before treating headaches in patients not previously diagnosed as migraineurs, and in migraineurs who present with symptoms atypical of migraine, other potentially serious neurological conditions need to be excluded. Frovatriptan succinate tablets are contraindicated in patients with a history of stroke or TIA [see Contraindications (4)].

5.5 Other Vasospasm Reactions

Frovatriptan, may cause non-coronary vasospastic reactions, such as peripheral vascular ischemia, gastrointestinal vascular ischemia and infarction (presenting with abdominal pain and bloody diarrhea), splenic infarction, and Raynaud’s syndrome. In patients who experience symptoms or signs suggestive of a vasospastic reaction following the use of any 5-HT1 agonist, rule out a vasospastic reaction before using frovatriptan [see Contraindications (4)].

Reports of transient and permanent blindness and significant partial vision loss have been reported with the use of 5-HT1 agonists. Since visual disorders may be part of a migraine attack, a causal relationship between these events and the use of 5-HT1 agonists have not been clearly established.

5.6 Medication Overuse Headache

Overuse of acute migraine drugs (e.g., ergotamine, triptans, opioids, or combination of these drugs for 10 or more days per month) may lead to exacerbation of headache (medication overuse headache). Medication overuse headache may present as migraine-like daily headaches or as a marked increase in frequency of migraine attacks. Detoxification of patients, including withdrawal of the overused drugs, and treatment of withdrawal symptoms (which often includes a transient worsening of headache) may be necessary.

5.7 Serotonin Syndrome

Serotonin syndrome may occur with frovatriptan, particularly during co-administration with selective serotonin reuptake inhibitors (SSRIs), serotonin norepinephrine reuptake inhibitors (SNRIs), tricyclic antidepressants (TCAs), and monoamine oxidase (MAO) inhibitors [see Drug Interactions (7.3)]. Serotonin syndrome symptoms may include mental status changes (e.g., agitation, hallucinations, coma), autonomic instability (e.g., tachycardia, labile blood pressure, hyperthermia), neuromuscular aberrations (e.g., hyperreflexia, incoordination), and/or gastrointestinal symptoms (e.g., nausea, vomiting, diarrhea). The onset of symptoms usually occurs within minutes to hours of receiving a new or a greater dose of a serotonergic medication. Discontinue frovatriptan if serotonin syndrome is suspected.

5.8 Increase in Blood Pressure

Significant elevation in blood pressure, including hypertensive crisis with acute impairment of organ systems, has been reported on rare occasions in patients treated with 5-HT1 agonists, including patients without a history of hypertension. Monitor blood pressure in patients treated with frovatriptan. Frovatriptan succinate tablets are contraindicated in patients with uncontrolled hypertension [see Contraindications (4)].

5.9 Hypersensitivity Reactions

There have been reports of reactions including anaphylaxis and angioedema, in patients receiving frovatriptan. Such reactions can be life threatening or fatal. In general, anaphylactic reactions to drugs are more likely to occur in individuals with a history of sensitivity to multiple allergens. Frovatriptan succinate tablets are contraindicated in patients with a history of hypersensitivity reaction to frovatriptan [see Contraindications (4)].

6 ADVERSE REACTIONS

The following serious adverse reactions are described elsewhere in other sections of the labeling:

- Myocardial Ischemia, Myocardial Infarction, and Prinzmetal’s Angina [see Warnings and Precautions (5.1)]
- Arrhythmias [see Warnings and Precautions (5.2)]
- Chest, Throat, Neck, and/or Jaw Pain/Tightness/Pressure [see Warnings and Precautions (5.3)]
- Cerebrovascular Events [see Warnings and Precautions (5.4)]
- Other Vasospasm Reactions [see Warnings and Precautions (5.5)]
- Medication Overuse Headache [see Warnings and Precautions (5.6)]
- Serotonin Syndrome [see Warnings and Precautions (5.7)]
- Increases in Blood Pressure [see Warnings and Precautions (5.8)]
- Hypersensitivity Reactions [see Contraindications (4) and Warnings and Precautions (5.8)]

6.1 Clinical Trials Experience

Because clinical trials are conducted under widely varying conditions, adverse reaction rates observed in the clinical trials of a drug cannot be directly compared to rates in the clinical trials of another drug and may not reflect the rates observed in practice.

Frovatriptan was evaluated in four randomized, double-blind, placebo-controlled, short-term trials. These trials involved 2392 patients (1554 on frovatriptan 2.5 mg and 838 on placebo). In these short-term trials, patients were predominately female (88%) and Caucasian (94%) with a mean age of 42 years (range 18 to 69).The treatment-emergent adverse events that occurred most frequently following administration of frovatriptan 2.5 mg (i.e., in at least 2% of patients), and at an incidence ≥1% greater than with placebo, were dizziness, paresthesia, headache, dry mouth, fatigue, flushing, hot or cold sensation, dyspepsia, skeletal pain, and chest pain. In a long-term, open-label study where 496 patients were allowed to treat multiple migraine attacks with frovatriptan 2.5 mg for up to 1 year, 5% of patients (n=26) discontinued due to treatment-emergent adverse events.

Table 1 lists treatment-emergent adverse events reported within 48 hours of drug administration that occurred with frovatriptan 2.5 mg at an incidence of ≥2% and more often than on placebo, in the four placebo-controlled trials. The events cited reflect experience gained under closely monitored conditions of clinical trials in a highly selected patient population. In actual clinical practice or in other clinical trials, these incidence estimates may not apply, as the conditions of use, reporting behavior, and the kinds of patients treated may differ.

Table 1: Adverse Reactions Reported within 48 Hours (Incidence ≥2% and Greater Than Placebo) of Patients in Four Pooled Placebo-Controlled Migraine Trials

Adverse Reactions | Frovatriptan 2.5 mg (n=1554) | Placebo (n=838)
Central & peripheral nervous system; Dizziness; Headache; Paresthesia | 8%; 4%; 4% | 5%; 3%; 2%
Gastrointestinal system disorders; Dry mouth; Dyspepsia | 3%; 2% | 1%; 1%
Body as a whole – general disorders; Fatigue; Hot or cold sensation; Chest pain | 5%; 3%; 2% | 2%; 2%; 1%
Musculo-skeletal; Skeletal pain | 3% | 2%
Vascular; Flushing | 4% | 2%

The incidence of adverse events in clinical trials did not increase when up to 3 doses were used within 24 hours. The incidence of adverse events in placebo-controlled clinical trials was not affected by gender, age, or concomitant medications commonly used by migraine patients. There were insufficient data to assess the impact of race on the incidence of adverse events.

Other Events Observed in Association with the Administration of Frovatriptan

The incidence of frequently reported adverse events in four placebo-controlled trials are presented below. Events are further classified within body system categories. Frequent adverse events are those occurring in at least 1/100 patients.

Central and peripheral nervous system: dysesthesia and hypoesthesia.

Gastrointestinal: vomiting, abdominal pain and diarrhea.

Body as a whole: pain.

Psychiatric: insomnia and anxiety.

Respiratory: sinusitis and rhinitis.

Vision disorders: vision abnormal.

Skin and appendages: sweating increased.

Hearing and vestibular disorders: tinnitus.

Heart rate and rhythm: palpitation.

6.2 Postmarketing Experience

The following adverse reactions were identified during post approval use of frovatriptan. Because these events are reported voluntarily from a population of uncertain size, it is not always possible to reliably estimate their frequency or establish a causal relationship to drug exposure.

Central and peripheral nervous system: Seizure.

7 DRUG INTERACTIONS

7.1 Ergot-containing Drugs

Ergot-containing drugs have been reported to cause prolonged vasospastic reactions. Because these effects may be additive, use of ergotamine-containing or ergot-type medications (like dihydroergotamine or methysergide) and frovatriptan within 24 hours of each other is contraindicated [see Contraindications (4)].

7.2 5-HT1B/1D Agonists

Because their vasospastic effects may be additive, co-administration of frovatriptan and other 5-HT1 agonists (e.g., triptans) within 24 hours of each other is contraindicated [see Contraindications (4)].

7.3 Selective Serotonin Reuptake Inhibitors / Serotonin Norepinephrine Reuptake Inhibitors and Serotonin Syndrome

Cases of serotonin syndrome have been reported during combined use of triptans and SSRIs, SNRIs, TCAs, and MAO inhibitors [see Warnings and Precautions (5.7)].

8 USE IN SPECIFIC POPULATIONS

8.1 Pregnancy

Risk Summary

There are no adequate data on the developmental risk associated with the use of frovatriptan in pregnant women. In animal studies, frovatriptan produced developmental toxicity (embryofetal lethality, fetal abnormalities, and decreased embryofetal growth) when administered to pregnant rats and rabbits at doses greater than those used clinically [see Animal Data].

In the U.S. general population, the estimated background risk of major birth defects and of miscarriage in clinically recognized pregnancies is 2% to 4% and 15% to 20%, respectively. The reported rate of major birth defects among deliveries to women with migraine ranged from 2.2% to 2.9% and the reported rate of miscarriage was 17%, which were similar to rates reported in women without migraine.

Clinical Considerations

Disease-Associated Maternal and/or Embryo/Fetal Risk

Published data have suggested that women with migraines may be at increased risk of preeclampsia during pregnancy.

Data

Animal Data

When pregnant rats were administered frovatriptan (oral doses of 0, 100, 500, or 1000 mg/kg/day) throughout organogenesis, increased embryofetal mortality and an increased incidence of fetal malformations were observed at the high dose; decreased fetal body weights and increased incidences of fetal structural variations associated with growth impairment were observed at all doses. The lowest effect dose for embryofetal developmental toxicity in rats (100 mg/kg/day) is approximately 130 times the maximum recommended human dose (MRHD) of 7.5 mg/day on a body surface area (mg/m^2) basis.

When pregnant rabbits were administered frovatriptan (oral doses of 0, 5, 20, or 80 mg/kg/day) throughout organogenesis, embryofetal mortality was increased at the mid and high doses. The no-effect dose for embryofetal developmental toxicity in rabbits (5 mg/kg/day) is approximately 13 times the MRHD on a mg/m^2 basis.

Oral administration of frovatriptan (0, 100, 500, or 1000 mg/kg/day) to female rats throughout pregnancy and lactation resulted in increased embryofetal mortality at the high dose. The no effect dose for pre- and postnatal developmental toxicity in rats (500 mg/kg/day) is approximately 650 times the MRHD on a mg/m^2 basis.

8.2 Lactation

Risk Summary

There are no data on the presence of frovatriptan in human milk, the effects of frovatriptan on the breastfed infant, or the effects of frovatriptan on milk production. In rats, oral dosing with frovatriptan resulted in levels of frovatriptan and/or its metabolites in milk up to four times higher than in plasma.

The developmental and health benefits of breastfeeding should be considered along with the mother’s clinical need for frovatriptan and any potential adverse effects on the breastfed infant from frovatriptan or from the underlying maternal condition.

8.4 Pediatric Use

The safety and effectiveness in pediatric patients have not been established. Therefore, frovatriptan is not recommended for use in patients under 18 years of age. There are no additional adverse reactions identified in pediatric patients based on postmarketing experience that were not previously identified in adults.

8.5 Geriatric Use

Mean blood concentrations of frovatriptan in elderly patients were 1.5 to 2 times higher than those seen in younger adults [see Clinical Pharmacology (12.3)]. No dosage adjustment is necessary.

8.6 Patients with Hepatic Impairment

No dosage adjustment is necessary when frovatriptan is given to patients with mild to moderate hepatic impairment.

There is no clinical or pharmacokinetic experience with frovatriptan in patients with severe hepatic impairment. Because a greater than two-fold increase in AUC is predicted in patients with severe hepatic impairment, there is a greater potential for adverse events in these patients, and frovatriptan should therefore be used with caution in that population.

10 OVERDOSAGE

The elimination half-life of frovatriptan is 26 hours [see Clinical Pharmacology (12.3)]. Therefore, monitoring of patients after overdose with frovatriptan should continue for at least 48 hours or while symptoms or signs persist. There is no specific antidote to frovatriptan. It is unknown what effect hemodialysis or peritoneal dialysis has on the serum concentrations of frovatriptan.

11 DESCRIPTION

Frovatriptan succinate tablets contain frovatriptan succinate, a selective 5-hydroxytryptamine1 (5-HT1B/1D) receptor subtype agonist, as the active ingredient. Frovatriptan succinate is chemically designated as R-(+) 3-methylamino-6-carboxamido-1,2,3,4-tetrahydrocarbazole monosuccinate monohydrate and it has the following structure:

The molecular formula is C18H23N3O5.H2O, representing a molecular weight of 379.4 g/mol. Frovatriptan succinate is a white to off-white powder that is soluble in water and very slightly soluble in methanol.

Each frovatriptan succinate tablet for oral administration contains 3.91 mg frovatriptan succinate, equivalent to 2.5 mg of frovatriptan base. Each tablet also contains the inactive ingredients anhydrous lactose, colloidal silicon dioxide, hypromellose, lactose monohydrate, magnesium stearate, microcrystalline cellulose, sodium starch glycolate (potato), talc, titanium dioxide and triacetin.

12 CLINICAL PHARMACOLOGY

12.1 Mechanism of Action

Frovatriptan binds with high affinity to 5-HT1B/1D receptors. The therapeutic activity of frovatriptan is thought to be due to the agonist effects at the 5-HT1B/1D receptors on intracranial blood vessels (including the arterio-venous anastomoses) and sensory nerves of the trigeminal system which result in cranial vessel constriction and inhibition of pro-inflammatory neuropeptide release.

12.3 Pharmacokinetics

The pharmacokinetics of frovatriptan are similar in migraine patients and healthy subjects.

Absorption

Mean maximum blood concentrations (Cmax) in patients are achieved approximately 2 to 4 hours after administration of a single oral dose of frovatriptan 2.5 mg. The absolute bioavailability of an oral dose of frovatriptan 2.5 mg in healthy subjects is about 20% in males and 30% in females. Food has no significant effect on the bioavailability of frovatriptan, but delays tmax by one hour.

Distribution

Binding of frovatriptan to serum proteins is low (approximately 15%). Reversible binding to blood cells at equilibrium is approximately 60%, resulting in a blood: plasma ratio of about 2:1 in both males and females. The mean steady state volume of distribution of frovatriptan following intravenous administration of 0.8 mg is 4.2 L/kg in males and 3 L/kg in females.

Metabolism

In vitro, cytochrome P450 1A2 appears to be the principal enzyme involved in the metabolism of frovatriptan. Following administration of a single oral dose of radiolabeled frovatriptan 2.5 mg to healthy male and female subjects, 32% of the dose was recovered in urine and 62% in feces. Radiolabeled compounds excreted in urine were unchanged frovatriptan, hydroxylated frovatriptan, N-acetyl desmethyl frovatriptan, hydroxylated N-acetyl desmethyl frovatriptan and desmethyl frovatriptan, together with several other minor metabolites. Desmethyl frovatriptan has lower affinity for 5-HT1B/1D receptors compared to the parent compound. The N-acetyl desmethyl metabolite has no significant affinity for 5-HT receptors. The activity of the other metabolites is unknown.

Elimination

After an intravenous dose, mean clearance of frovatriptan was 220 and 130 mL/min in males and females, respectively. Renal clearance accounted for about 40% (82 mL/min) and 45% (60 mL/min) of total clearance in males and females, respectively. The mean terminal elimination half-life of frovatriptan in both males and females is approximately 26 hours.

Special Populations

Hepatic Impairment

The AUC of frovatriptan in patients with mild (Child-Pugh 5 to 6) to moderate (Child-Pugh 7 to 9) hepatic impairment was about twice that of young, healthy subjects, but within the range observed in healthy elderly subjects and was considerably lower than the values attained with higher doses of frovatriptan (up to 40 mg), which were not associated with any serious adverse effects. There is no clinical or pharmacokinetic experience with frovatriptan in patients with severe hepatic impairment.

Renal Impairment

The pharmacokinetics of frovatriptan following a single oral dose of 2.5 mg was not different in patients with renal impairment (5 males and 6 females, creatinine clearance 16 to 73 mL/min) compared to subjects with normal renal function.

Age

Mean AUC of frovatriptan was 1.5- to 2-fold higher in healthy elderly subjects (age 65 to 77 years) compared to those in healthy younger subjects (age 21 to 37 years). There was no difference in tmax or t1/2 between the two populations.

Sex

There was no difference in the mean terminal elimination half-life of frovatriptan in males and females. Bioavailability was higher, and systemic exposure to frovatriptan was approximately 2-fold greater, in females than males, irrespective of age.

Race

The effect of race on the pharmacokinetics of frovatriptan has not been examined.

Drug Interaction Studies

Frovatriptan is not an inhibitor of human monoamine oxidase (MAO) enzymes or cytochrome P450 (isozymes 1A2, 2C9, 2C19, 2D6, 2E1, 3A4) in vitro at concentrations up to 250 to 500- fold higher than the highest blood concentrations observed in man at a dose of 2.5 mg. No induction of drug metabolizing enzymes was observed following multiple dosing of frovatriptan to rats or on addition to human hepatocytes in vitro. Although no clinical trials have been performed, it is unlikely that frovatriptan will affect the metabolism of co-administered drugs metabolized by these mechanisms.

Oral Contraceptives

Retrospective analysis of pharmacokinetic data from females across trials indicated that the mean Cmax and AUC of frovatriptan are 30% higher in those subjects taking oral contraceptives compared to those not taking oral contraceptives.

Ergotamine

The AUC and Cmax of frovatriptan (2 × 2.5 mg dose) were reduced by approximately 25% when co-administered with ergotamine tartrate [see Contraindications (4), Drug Interactions (7.1)].

Propranolol

Propranolol increased the AUC of frovatriptan 2.5 mg in males by 60% and in females by 29%. The Cmax of frovatriptan was increased 23% in males and 16% in females in the presence of propranolol. The tmax as well as half-life of frovatriptan, though slightly longer in the females, were not affected by concomitant administration of propranolol.

Moclobemide

The pharmacokinetic profile of frovatriptan was unaffected when a single oral dose of frovatriptan 2.5 mg was administered to healthy female subjects receiving the MAO-A inhibitor, moclobemide, at an oral dose of 150 mg twice a day for 8 days.

13 NONCLINICAL TOXICOLOGY

13.1 Carcinogenesis, Mutagenesis, Impairment of Fertility

Carcinogenesis

The carcinogenic potential of orally administered frovatriptan was evaluated in an 84-week study in mice (4, 13, and 40 mg/kg/day), a 104-week study in rats (8.5, 27, and 85 mg/kg/day), and a 26-week study in p53(+/-) transgenic mice (20, 62.5, 200, and 400 mg/kg/day). Although a maximum tolerated dose was not achieved in the 84-week mouse study and in female rats, plasma exposures at the highest doses studied were higher than that achieved in humans at the MRHD of 7.5 mg/day. There were no increases in tumor incidence in the 84-week mouse study at doses producing plasma exposures (AUC) 140 times that in humans at the MRHD. In the rat study, there was a statistically significant increase in the incidence of pituitary adenomas in males only at 85 mg/kg/day, a dose associated with a plasma AUC 250 times that in humans at the MRHD. In the 26-week p53(+/-) transgenic mouse study, the incidence of subcutaneous sarcomas was increased in females at doses of 200 and 400 mg/kg/day.

These sarcomas were associated with subcutaneously implanted animal identification transponders, and are not considered to be relevant to humans. There were no other increases in tumor incidence of any type in any dose group.

Mutagenesis

Frovatriptan was clastogenic in human lymphocyte cultures, in the absence of metabolic activation. In the bacterial reverse mutation assay (Ames test), frovatriptan produced an equivocal response in the absence of metabolic activation. Frovatriptan was negative in an in vitro mouse lymphoma tk assay and an in vivo mouse bone marrow micronucleus test.

Impairment of Fertility

Male and female rats were dosed orally with frovatriptan prior to and during mating and in females up to implantation, at doses of 100, 500, and 1000 mg/kg/day (equivalent to approximately 130, 650, and 1300 times the MRHD on a mg/m^2 basis). At all dose levels, there was an increase in the number of females that mated on the first day of pairing compared to control animals. This occurred in conjunction with a prolongation of the estrous cycle. In addition, females had a decreased mean number of corpora lutea, and consequently a lower number of live fetuses per litter, which suggested a partial impairment of ovulation. There were no other fertility-related effects.

14 CLINICAL STUDIES

The efficacy of frovatriptan in the acute treatment of migraine headaches was demonstrated in four randomized, double-blind, placebo-controlled, short-term outpatient trials. In these trials, patients received doses of frovatriptan from 0.5 mg to 40 mg. In these controlled short-term trials, patients were predominately female (88%) and Caucasian (94%) with a mean age of 42 years (range 18 to 69). Patients were instructed to treat a moderate to severe headache. Headache response, defined as a reduction in headache severity from moderate or severe pain to mild or no pain, was assessed for up to 24 hours after dosing. The associated symptoms nausea, vomiting, photophobia, and phonophobia were also assessed. Maintenance of response was assessed for up to 24 hours post dose. In two of the trials a second dose of frovatriptan was provided after the initial treatment, to treat recurrence of the headache within 24 hours. Other medication, excluding other 5-HT1 agonists and ergotamine containing compounds, was permitted from 2 hours after the first dose of frovatriptan. The frequency and time to use of additional medications were also recorded.

In all four placebo-controlled trials, the percentage of patients achieving a headache response 2 hours after treatment was significantly greater for those taking frovatriptan 2.5 mg compared to those taking placebo (Table 2).

Lower doses of frovatriptan (1 mg or 0.5 mg) were not effective at 2 hours. Higher doses (5 mg to 40 mg) of frovatriptan showed no added benefit over 2.5 mg but did cause a greater incidence of adverse events.

Table 2: Percentage of Patients with Headache Response (Mild or No Headache) 2 Hours Following Treatmenta

Study | Frovatriptan 2.5 mg | Placebo
1 | 42%* (n=90) | 22% (n=91)
2 | 39%* (n=187) | 21% (n=99)
3 | 46%** (n=672) | 27% (n=347)
4 | 37%** (n=438) | 23% (n=225)
a ITT observed data, excludes patients who had missing data or were asleep.
*p<0.05.
**p<0.001 in comparison with placebo.

The estimated probability of achieving an initial headache response by 2 hours following treatment is depicted in Figure 1.

Figure 1: Estimated Probability of Achieving Initial Headache Response Within 2 Hours

Figure 1 shows a Kaplan-Meier plot of the probability over time of obtaining headache response (no or mild pain) following treatment with frovatriptan 2.5 mg or placebo. The probabilities displayed are based on pooled data from the four placebo-controlled trials described in Table 2. Patients who did not achieve a response were censored at 24 hours.

In patients with migraine-associated nausea, photophobia, and phonophobia at baseline there was a decreased incidence of these symptoms in frovatriptan treated patients compared to placebo.

The estimated probability of patients taking a second dose or other medication for their migraine over the 24 hours following the initial dose of study treatment is summarized in Figure 2.

Figure 2: Estimated Probability of Patients Taking a Second Dose or Other Medication for Migraine Over the 24 Hours Following the Initial Dose of Study Treatment

Figure 2 is a Kaplan-Meier plot showing the probability of patients taking a second dose or other medication for migraine over the 24 hours following the initial dose of study medication based on the data from the four placebo-controlled trials described in Table 2. The plot includes those patients who had a response to the initial dose and those who did not. The protocols did not permit remedication within 2 hours of the initial dose.

Efficacy was unaffected by a history of aura; gender; age, or concomitant medications commonly used by migraine patients.

16 HOW SUPPLIED/STORAGE AND HANDLING

Frovatriptan succinate tablets, containing 2.5 mg of frovatriptan (base) as the succinate, are available as white to off-white, circular biconvex film-coated tablets, debossed with ‘72’ on one side and ‘G’ on the other side. The tablets are available in:

Blister card of 9 tablets (NDC 68462-694-40), 1 blister card per carton (NDC 68462-694-97)

Store at 20°C to 25°C (68°F to 77°F); excursions permitted to 15°C to 30°C (59°F to 86°F) [see USP Controlled Room Temperature]. Protect from moisture.

17 PATIENT COUNSELING INFORMATION

Advise the patient to read the FDA-approved patient labeling (Patient Information).

Myocardial Ischemia and/or Infarction, Prinzmetal’s Angina, Other Vasospastic Reactions, and Cerebrovascular Events

Inform patients that frovatriptan may cause serious cardiovascular adverse reactions such as myocardial infarction or stroke, which may result in hospitalization and even death. Although serious cardiovascular reactions can occur without warning symptoms, instruct patients to be alert for the signs and symptoms of chest pain, shortness of breath, weakness, slurring of speech, and instruct them to ask for medical advice when observing any indicative sign or symptoms. Instruct patients to seek medical advice if they have symptoms of other vasospastic reactions [see Warnings and Precautions (5.1, 5.2, 5.4, 5.5, and 5.8)].

Hypersensitivity Reactions

Inform patients that anaphylactic reactions have occurred in patients receiving frovatriptan. Inform patients that such reactions can be life threatening or fatal and to seek immediate medical attention if they have anaphylactic symptoms. In general, anaphylactic reactions to drugs are more likely to occur in individuals with a history of sensitivity to multiple allergens [see Contraindications (4)].

Medication Overuse Headache

Inform patients that use of drugs to treat acute migraines for 10 or more days per month may lead to an exacerbation of headache, and encourage patients to record headache frequency and drug use (e.g., by keeping a headache diary) [see Warnings and Precautions (5.6)].

Serotonin Syndrome

Inform patients about the risk of serotonin syndrome with the use of frovatriptan or other triptans, particularly during combined use with SSRIs, SNRIs, TCAs, and MAO inhibitors [see Warnings and Precautions (5.7) and Drug Interactions (7.3)].

Pregnancy

Advise patients to notify their healthcare provider if they become pregnant during treatment or plan to become pregnant [see Use in Specific Populations (8.1)].

Lactation

Inform patients to notify their healthcare provider if they are breastfeeding or plan to breastfeed [see Use in Specific Populations (8.2)].

Distributed by:

Glenmark Pharmaceuticals Inc., USA
Elmwood Park, NJ 07407

Questions? 1(888)721-7115

www.glenmarkpharma-us.com

May 2025

PATIENT INFORMATION

FROVATRIPTAN SUCCINATE

(froe″ va trip′ tan sux′ i nate)

TABLETS

What is the most important information I should know about frovatriptan succinate tablets?

Frovatriptan succinate tablets can cause serious side effects, including:

- Heart attack and other heart problems. Heart problems may lead to death. Stop taking frovatriptan succinate tablets and get emergency medical help right away if you have any of the following symptoms of a heart attack:
- discomfort in the center of your chest that lasts for more than a few minutes, or that goes away and comes back
- severe tightness, pain, pressure, or heaviness in your chest, throat, neck, or jaw
- pain or discomfort in your arms, back, neck, jaw, or stomach
- shortness of breath with or without chest discomfort
- breaking out in a cold sweat
- nausea or vomiting
- feeling lightheaded
Frovatriptan succinate tablets are not for people with risk factors for heart disease unless a heart exam is done and shows no problem. You have a higher risk for heart disease if you:

- have high blood pressure

- have high cholesterol levels

- smoke

- are overweight

- have diabetes

- have a family history of heart disease

What are frovatriptan succinate tablets?

Frovatriptan succinate tablets are a prescription medicine used to treat migraine headaches with or without aura in adults.

Frovatriptan succinate tablets are not used to treat other types of headaches.

Frovatriptan succinate tablets are not used to prevent or decrease the number of migraine headaches.

It is not known if frovatriptan succinate tablets are safe and effective to treat cluster headaches.

It is not known if frovatriptan succinate tablets are safe and effective in children under 18 years of age.

Who should not take frovatriptan succinate tablets?

Do not take frovatriptan succinate tablets if you have:

- heart problems, a history of heart problems, or problems with the electrical system of your heart.
- had a stroke, transient ischemic attacks (TIAs), or problems with your blood circulation.
- had hemiplegic migraines or basilar migraines. If you are not sure if you have had these types of migraines, ask your healthcare provider.
- narrowing of blood vessels to your legs, arms, or stomach (peripheral vascular disease).
- injury to your bowel (intestine) due to poor blood circulation (ischemic bowel disease).
- uncontrolled high blood pressure.
- taken any of the following medicines in the last 24 hours:
  - almotriptan (AXERT®)
  - eletriptan (RELPAX®)
  - naratriptan (AMERGE®)
  - rizatriptan (MAXALT®, MAXALT-MLT®)
  - sumatriptan (IMITREX®, IMITREX STATDOSE, ONZETRA™ XSAIL™, ZEMBRACE™ SYMTOUCH™)
  - sumatriptan and naproxen (TREXIMET®)
  - zolmitriptan (ZOMIG®, ZOMIG-ZMT)
  - ergotamine or ergotamine-type medicines (CAFERGOT®, ERGOMAR®, D.H.E.45®, MIGRANAL®, MIGERGOT)
    Ask your healthcare provider if you are not sure if your medicine is listed above.
- an allergy to frovatriptan or any of the ingredients in frovatriptan succinate tablets. See the end of this leaflet for a complete list of ingredients in frovatriptan succinate tablets.

What should I tell my doctor before taking frovatriptan succinate tablets?

Before you take frovatriptan succinate tablets, tell your doctor about all of your medical conditions, including if you:

- have high blood pressure
- have high cholesterol
- have diabetes
- have liver problems
- smoke
- are overweight
- have heart disease or a family history of heart disease or stroke
- have any allergies
- are pregnant or plan to become pregnant. It is not known if frovatriptan succinate can harm your unborn baby
- are breastfeeding or plan to breastfeed. It is not known if frovatriptan succinate passes into your breast milk. Talk to your doctor about the best way to feed your baby if you take frovatriptan succinate tablets

Tell your doctor about all the medicines you take, including prescription and over-the-counter medicines, vitamins, and herbal supplements.

Frovatriptan succinate tablets and certain other medicines can affect each other, causing serious side effects.

Especially tell your doctor if you take:

- ergotamine or triptan medicine
- opioid pain medicine
- antidepressant medicines called:
- selective serotonin reuptake inhibitors (SSRIs)
- serotonin norepinephrine reuptake inhibitors (SNRIs)
- tricyclic antidepressants (TCAs)
- monoamine oxidase inhibitors (MAOIs)

Ask your doctor or pharmacist for a list of these medicines if you are not sure.

Know the medicines you take. Keep a list of them to show your doctor or pharmacist when you get a new medicine.

How should I take frovatriptan succinate tablets?

- Certain people should take their first dose of frovatriptan succinate tablets in their doctor’s office or in another medical setting. Ask your doctor if you should take your first dose in a medical setting.
- Take frovatriptan succinate tablets exactly as your doctor tells you.
- Take frovatriptan succinate tablets by mouth with fluids.
- If you do not get any relief from your headache after your first frovatriptan succinate tablet, do not take a second tablet without first talking with your doctor.
- If your headache comes back or you only get some relief from your headache, you may take a second frovatriptan succinate tablet if it has been at least 2 hours after the first tablet.
- Do not take more than 3 frovatriptan succinate tablets in a 24-hour period.
- It is not known if it is safe to take frovatriptan succinate tablets for more than 4 headaches in 30 days.
- If you take too many frovatriptan succinate tablets, call your doctor or go to the nearest hospital emergency room right away.
- You should write down when you have headaches and when you take frovatriptan succinate tablets so you can talk with your doctor about how frovatriptan succinate tablets are working for you.

What should I avoid while taking frovatriptan succinate tablets?

Frovatriptan succinate tablets can cause dizziness, weakness, or drowsiness. If you have these symptoms do not drive a car, use machinery, or do anything where you need to be alert.

What are the possible side effects of frovatriptan succinate tablets?

Frovatriptan succinate tablets can cause serious side effects.

See “What is the most important information I should know about frovatriptan succinate tablets?”

- Stroke. Stop taking frovatriptan succinate tablets and get emergency medical help right away if you have any of the following symptoms of a stroke:

- face drooping

- unusual weakness or numbness

- slurred speech

- Changes in color or sensation in your fingers and toes (Raynaud’s syndrome).
- Stomach and intestinal problems (gastrointestinal and colonic ischemic events). Symptoms of gastrointestinal and colonic ischemic events include:

- sudden or severe stomach pain

- constipation or diarrhea

- stomach pain after meals

- bloody diarrhea

- weight loss

- fever

- nausea or vomiting

- Problems with blood circulation to your legs and feet (peripheral vascular ischemia). Symptoms of peripheral vascular ischemia include:

- cramping and pain in your legs or hips

- numbness, tingling, or weakness in your legs

- feeling of heaviness or tightness in your leg muscles

- cold feeling or color changes in one or both legs or feet

- burning or aching pain in your feet or toes while resting

- Medication overuse headache. Some people who use too many frovatriptan succinate tablets may have worse headaches (medication overuse headache). If your headaches get worse, your doctor may decide to stop your treatment with frovatriptan succinate tablets.
- Serotonin syndrome. Serotonin syndrome is a rare but serious problem that can happen in people using frovatriptan succinate tablets, especially if frovatriptan succinate tablets are used with anti-depressant medicines called SSRIs, SNRIs, TCAs, and MAOIs. Call your doctor right away if you have any of the following symptoms of serotonin syndrome:

- mental changes such as seeing things that are not there (hallucinations), agitation, or coma

- high body temperature

- fast heartbeat

- tight muscles

- changes in blood pressure

- trouble walking

- Increased blood pressure.
- Allergic reactions. Call your doctor or get emergency medical help right away if you have symptoms of an allergic reaction, including:

- rash

- swelling of the face, mouth, throat, or tongue

- hives

- difficulty breathing

- itching

The most common side effects of frovatriptan succinate tablets are:

- dizziness

- dry mouth

- fatigue (tiredness, drowsiness)

- feeling hot or cold

- headache (other than a migraine headache)

- pain in joints or bones

- tingling or numbness in your fingers or toes

- chest pain

- warm, hot, burning feeling of your face (flushing)

- indigestion

These are not all the possible side effects of frovatriptan succinate tablets. For more information, ask your doctor or pharmacist. Call your doctor for medical advice about side effects. You may report side effects to FDA at 1-800-FDA-1088.

How should I store frovatriptan succinate tablets?

- Store frovatriptan succinate tablets at 68°C to 77°F (20°F to 25°C).
- Protect frovatriptan succinate tablets from moisture.
- Throw away (discard) after expiration date printed on the carton.

Keep frovatriptan succinate and all medicines out of the reach of children.

General information about the safe and effective use of frovatriptan succinate.

Medicines are sometimes prescribed for purposes other than those listed in a Patient Information leaflet. Do not use frovatriptan succinate tablets for a condition for which it was not prescribed. Do not give frovatriptan succinate tablets to other people, even if they have the same symptoms that you have. It may harm them. You can ask your doctor or pharmacist for information about frovatriptan succinate tablets that is written for health professionals.

You can also call Glenmark Pharmaceuticals Inc., USA at 1 (888) 721-7115.

What are the Ingredients in frovatriptan succinate tablets?

Active ingredient: frovatriptan succinate

Inactive ingredients: anhydrous lactose, colloidal silicon dioxide, hypromellose, lactose monohydrate, magnesium stearate, microcrystalline cellulose, sodium starch glycolate (potato), talc, titanium dioxide and triacetin.

Distributed by:

Glenmark Pharmaceuticals Inc., USA
Elmwood Park, NJ 07407

Questions? 1(888) 721-7115
www.glenmarkpharma-us.com

May 2025

Trademarks are the property of their respective owners.

Package/Label Display Panel

NDC 68462-694-97

Frovatriptan Succinate Tablets
2.5 mg